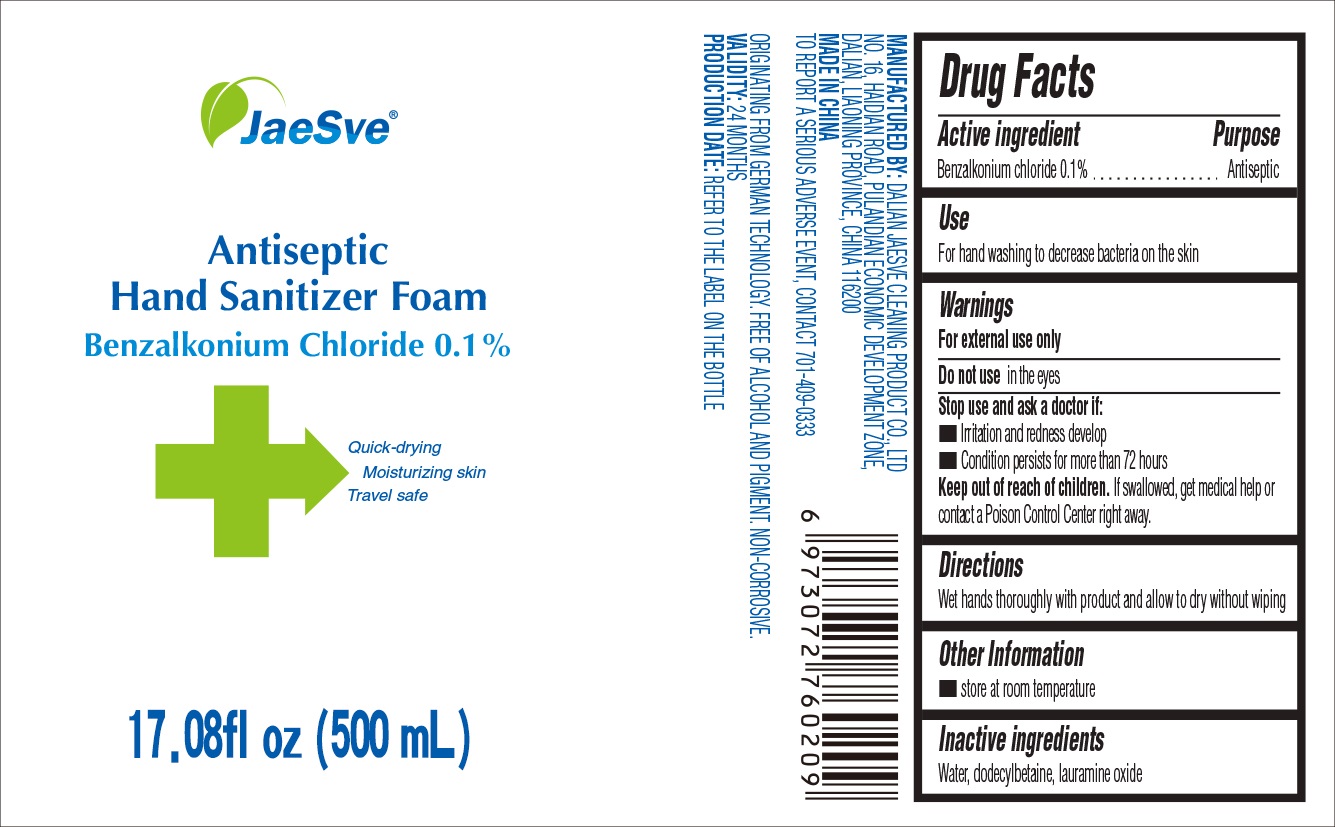 DRUG LABEL: Antiseptic Hand Sanitizer Foam
NDC: 77624-001 | Form: SOLUTION
Manufacturer: DaLian Jaesve Cleaning Product Co., Ltd
Category: otc | Type: HUMAN OTC DRUG LABEL
Date: 20200609

ACTIVE INGREDIENTS: BENZALKONIUM CHLORIDE 1 mg/1 mL
INACTIVE INGREDIENTS: WATER; LAURYL BETAINE; LAURAMINE OXIDE

Antiseptic Hand Sanitizer Foam

Active ingredient

Benzalkonium chloride 0.1%

Purpose

Antiseptic

Use

For hand washing to decrease bacteria on the skin

Warnings

For external use only

Do not use

in the eyes

Stop use and ask a doctor if:

- Irritation and redness develop
- Condition persists for more than 72 hours

Keep out of reach of children.

If swallowed, get medical help or contact a Poison Control Center right away.

Directions

Wet hands thoroughly with product and allow to dry without wiping

Other Information

- store at room temperature

Inactive ingredients

Water, dodecylbetaine, lauramine oxide